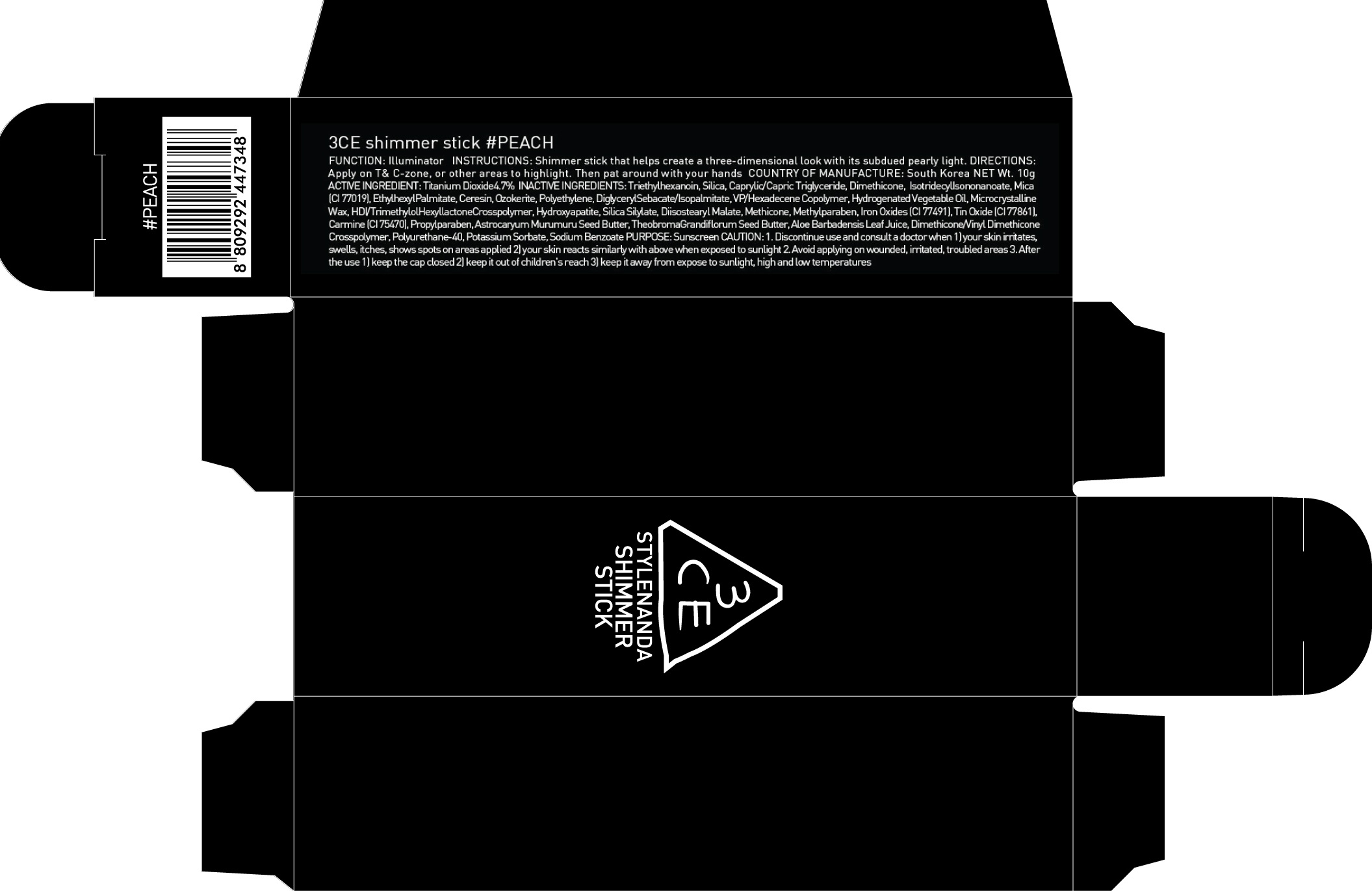 DRUG LABEL: 3CE SHIMMER PEACH
NDC: 60764-012 | Form: STICK
Manufacturer: Nanda Co., Ltd
Category: otc | Type: HUMAN OTC DRUG LABEL
Date: 20160920

ACTIVE INGREDIENTS: Titanium Dioxide 0.47 g/10 g
INACTIVE INGREDIENTS: Triethylhexanoin; Dimethicone

ACTIVE INGREDIENT

Active Ingredient: Titanium Dioxide 4.7%

INACTIVE INGREDIENT

Inactive Ingredients: Triethylhexanoin, Silica, Caprylic/Capric Triglyceride, Dimethicone, IsotridecylIsononanoate, Mica (CI 77019), EthylhexylPalmitate, Ceresin, Ozokerite, Polyethylene, DiglycerylSebacate/Isopalmitate, VP/Hexadecene Copolymer, Hydrogenated Vegetable Oil, Microcrystalline Wax, HDI/TrimethylolHexyllactoneCrosspolymer, Hydroxyapatite, Silica Silylate, Diisostearyl Malate, Methicone, Methylparaben, Iron Oxides (CI 77491), Tin Oxide (CI 77861), Carmine (CI 75470), Propylparaben, AstrocaryumMurumuru Seed Butter, TheobromaGrandiflorum Seed Butter, Aloe Barbadensis Leaf Juice, Dimethicone/Vinyl DimethiconeCrosspolymer, Polyurethane-40, Potassium Sorbate, Sodium Benzoate

PURPOSE

Purpose: Sunscreen

CAUTION

CAUTION: 1. Discontinue use and consult a doctor when - your skin irritates, swells, itches, shows spots on areas applied - your skin reacts similarly with above when exposed to sunlight 2. Avoid applying on wounded, irritated, troubled areas 3. After the use - keep the cap closed - keep it out of children's reach - keep it away from expose to sunlight, high and low temperatures

DESCRIPTION

INSTRUCTIONS: Shimmer stick that helps create a three-dimensional look with its subdued pearly light.

Directions: Apply on T& C-zone, or other areas to highlight. Then pat around with your hands